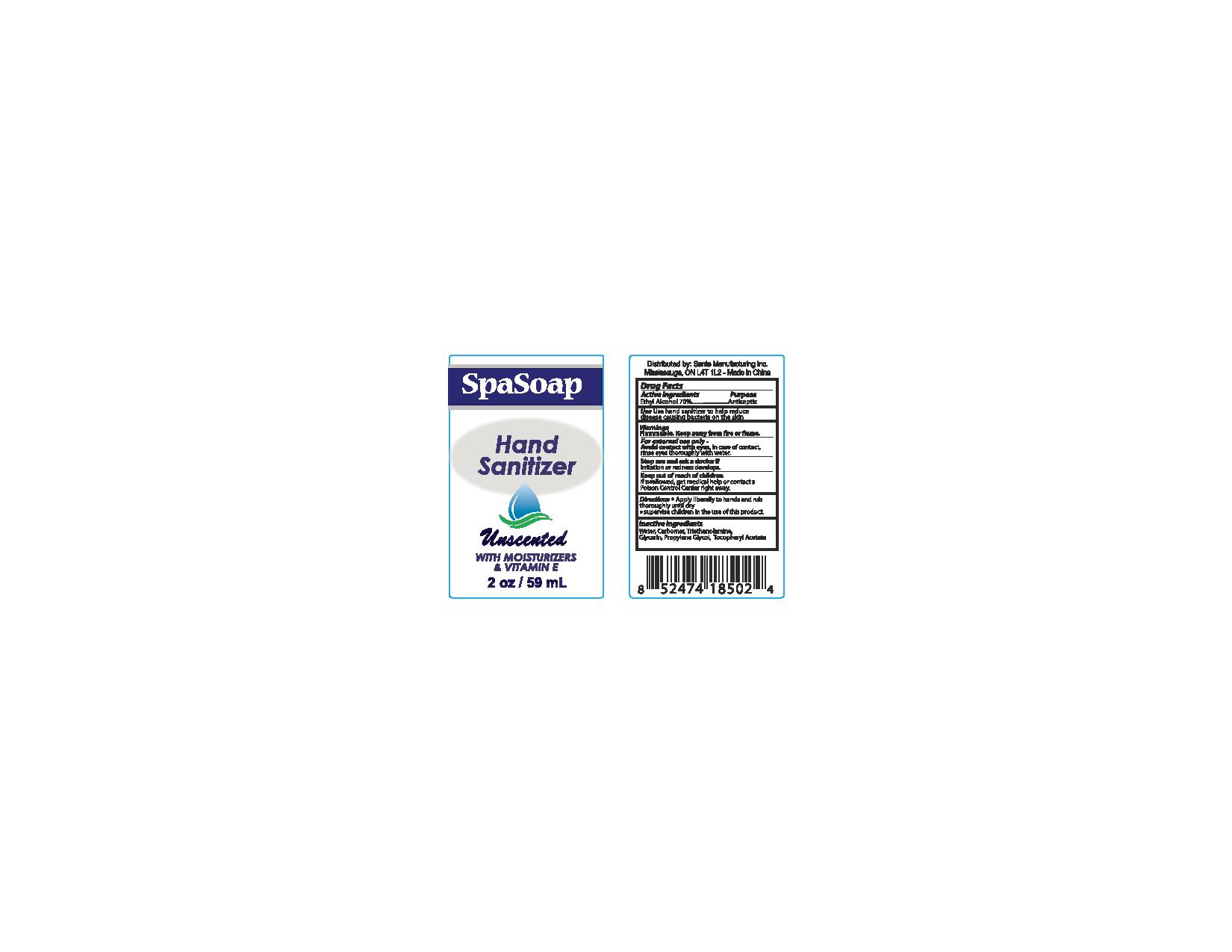 DRUG LABEL: Unscented
NDC: 71020-011 | Form: LIQUID
Manufacturer: Sante Maufacturing Inc
Category: otc | Type: HUMAN OTC DRUG LABEL
Date: 20170311

ACTIVE INGREDIENTS: ALCOHOL 700 mL/1000 mL
INACTIVE INGREDIENTS: WATER; CARBOMER 940; GLYCERIN; .ALPHA.-TOCOPHEROL ACETATE

Active Ingredients - Ethyl Alcohol 70%

Purpose - Antiseptic

INDICATIONS AND USAGE

Use hand sanitizer to help reduce disease causing bacteria on teh skin

WARNINGS

Flammable

OTHER SAFETY INFORMATION

keep Away from fire or flame

WHEN USING

For external use only -

USER SAFETY WARNINGS

Avoid contact with eyes in case of contact, rinse eyes thoroughly with water

Stop use and ask a doctor if irritation or redness develops

Keep out of reach of children

If swallowd, get medical help or contact a Poison Control Center right away.

Directions

- Apply liberally to hands and rub thoroughly until dry
- supervise children in the use of this product

Inactive Ingredients

water, carbomer, triethanolamine, glycerin, propylene glycol, tocopheryl acetate

PACKAGE LABEL

Spasoap

Hand Sanitizer

Unscented with moisturizers & vitamin E

2oz / 59ml